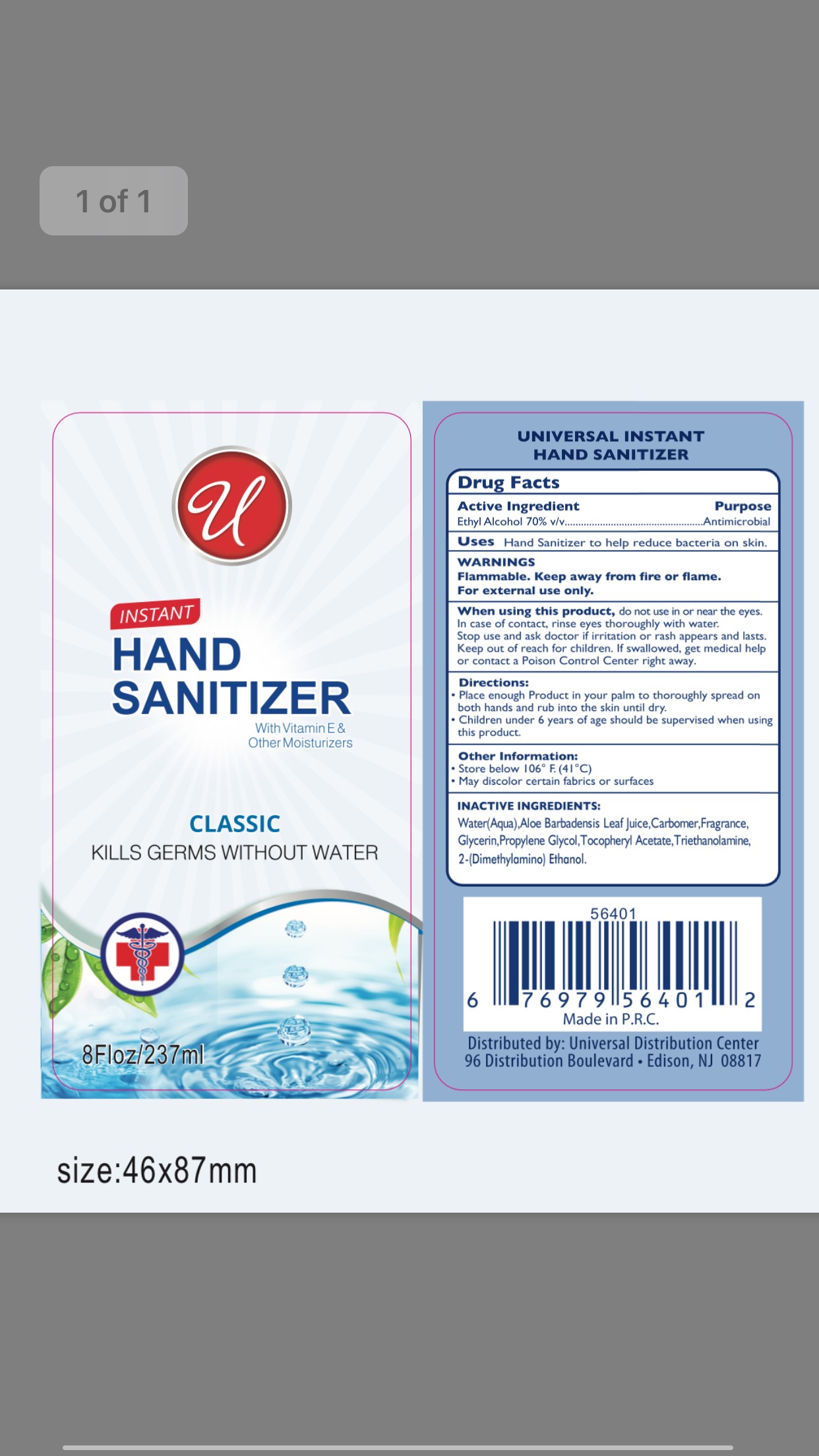 DRUG LABEL: U Instant Hand Sanitizer Classic
NDC: 75112-006 | Form: SOLUTION
Manufacturer: Zhejiang Shenying Technology Co., Ltd. Jiaojiang Branch
Category: otc | Type: HUMAN OTC DRUG LABEL
Date: 20200815

ACTIVE INGREDIENTS: ALCOHOL 70 mL/100 mL
INACTIVE INGREDIENTS: GLYCERIN; WATER; CARBOMER 940; ALPHA-TOCOPHEROL ACETATE; TROLAMINE; ALOE VERA LEAF; PROPYLENE GLYCOL

Active Ingredient(s)

Ethyl Alcohol 70%

Purpose

Antimicrobial

Use

Hand sanitizer to help reduce bacteria on the skin

Warnings

For external use only

Flammable. Keep away from fire or flame

When using this product do not use in or near eyes. In case of eye contact, rinse eyes thoroughly with water.

Stop use and ask a doctor if irritation or rash appears and lasts

Keep out of reach of children. If swallowed, get medical help or contact a Poison Control Center right away.

Directions

Place enough product in your palm to thoroughly spread on both hands and rub into skin untill dry

Children under six years of age should be supervised when using this product

Other information

Store below 106F (41C)

May discolor certain fabrics or surfaces

Inactive ingredients

Water, aloe barbadensis leaf jiuce, carbomer, fragrance, glycerin, propylene glycol, triethanolamine, tocopheryl acetate, 2-(dimethylamino) ethanol